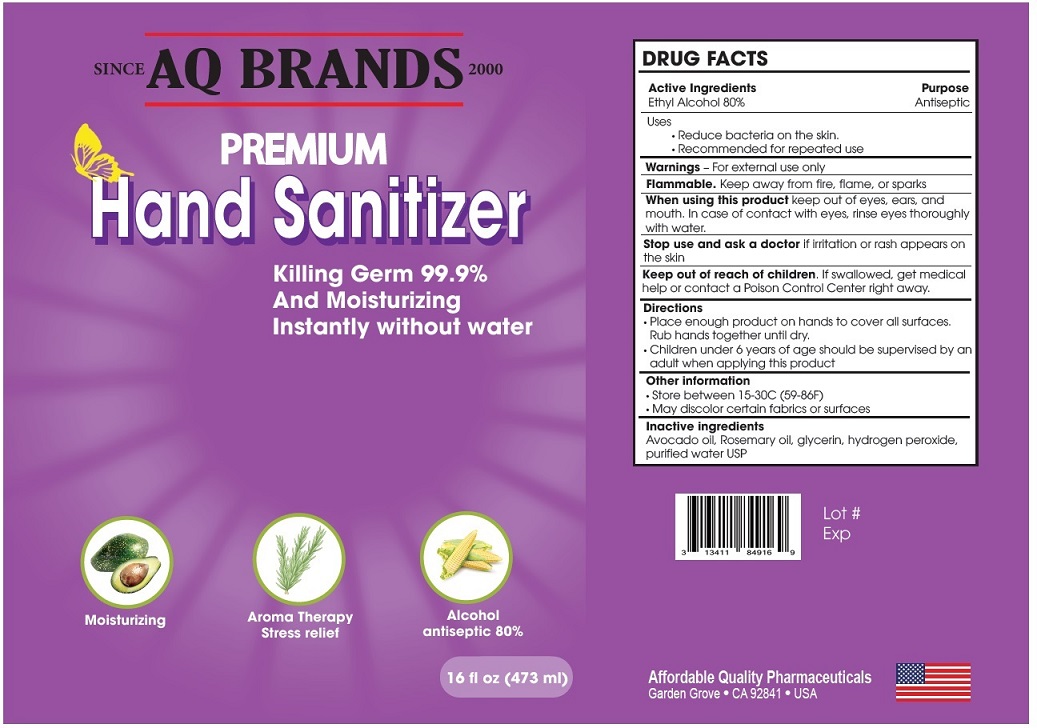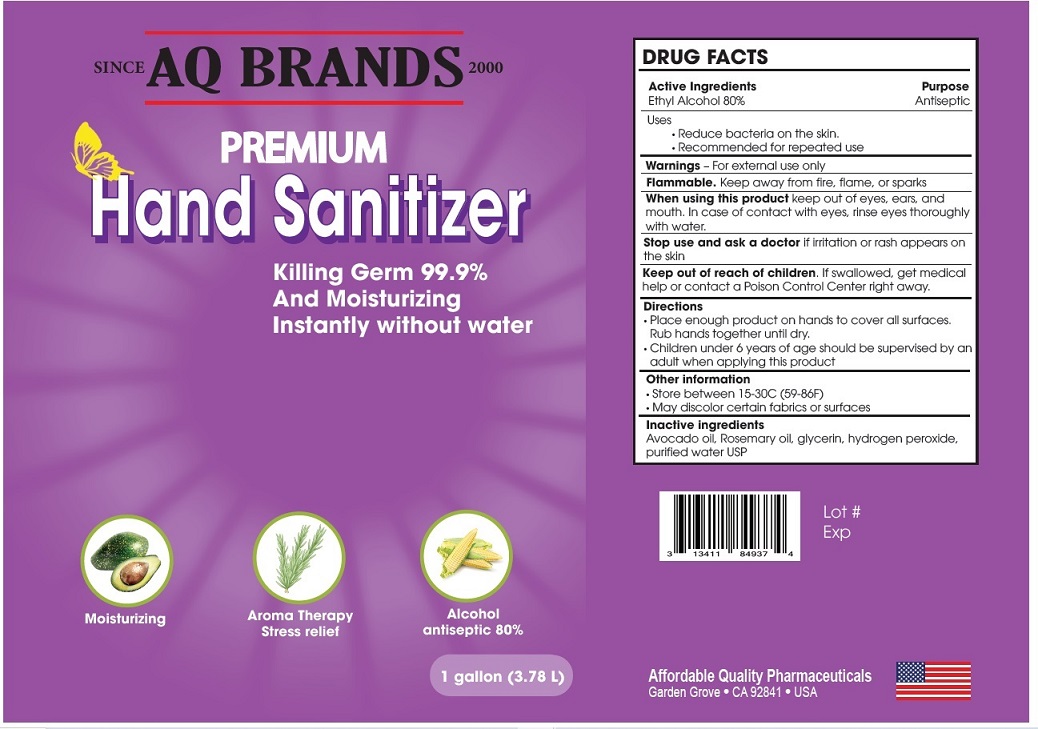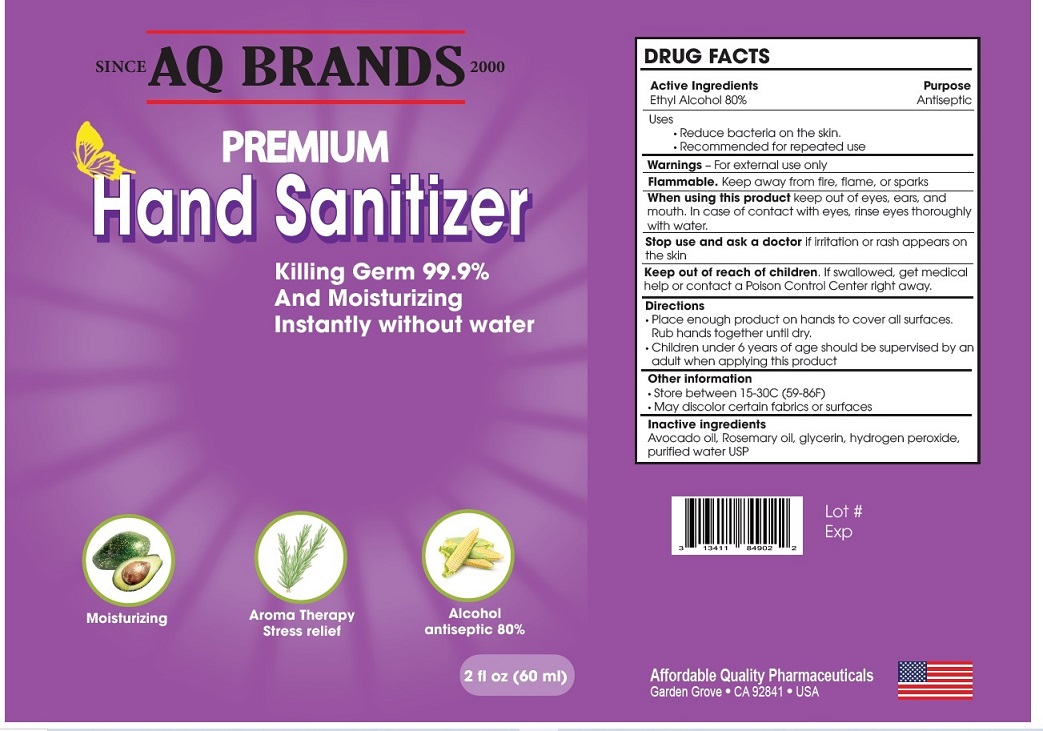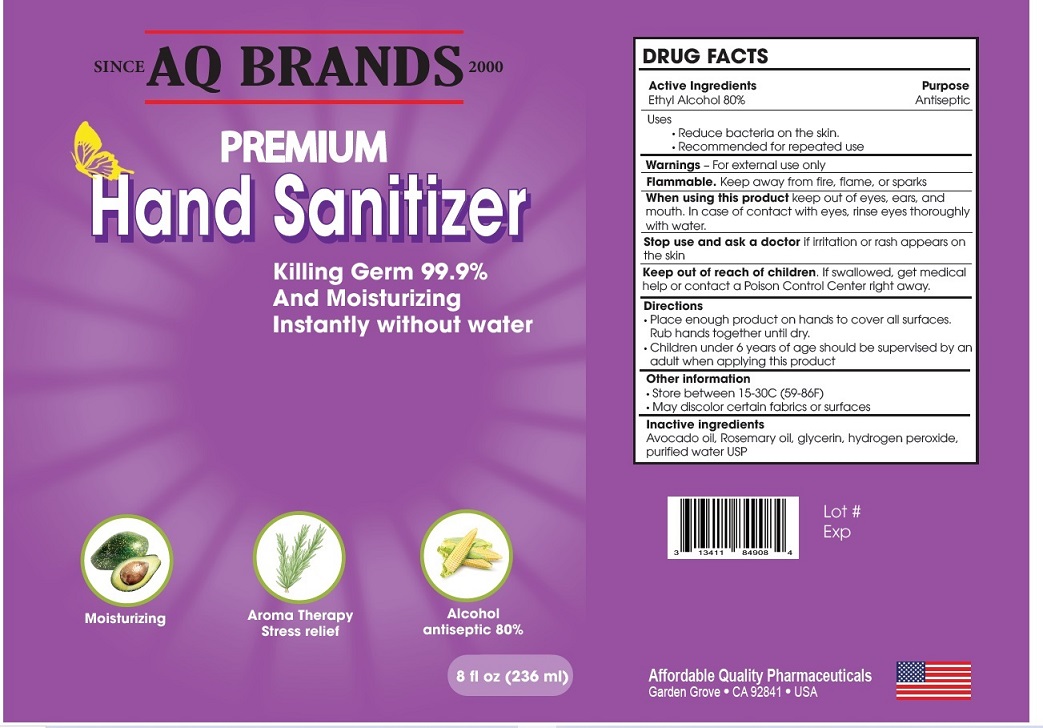 DRUG LABEL: PREMIUM HAND SANITIZER
NDC: 13411-849 | Form: LIQUID
Manufacturer: ADVANCED PHARMACEUTICAL SERVICES, INC. DBA AFFORDABLE QUALITY PHARMACEUTICALS
Category: otc | Type: HUMAN OTC DRUG LABEL
Date: 20200520

ACTIVE INGREDIENTS: ALCOHOL 8 mL/1 mL
INACTIVE INGREDIENTS: AVOCADO OIL; Glycerin; ROSEMARY OIL; HYDROGEN PEROXIDE; Water

PREMIUM HAND SANITIZER

Active Ingredient

Ethyl Alcohol 80%

Purpose

Antiseptic

Warnings

For external use only

Flammable. Keep away from fire, flame, or sparks

When using this product keep out of eyes, ears, and mouth.

In case of contact with eyes, rinse eyes thoroughly with water.

Stop use and ask a doctor if irritation or rash appears on the skin.

Uses

- Reduce bacteria on the skin.
- Recommended for repeated use

Directions

- Place enough product on hands to cover all surfaces. Rub hands together until dry.
- Children under 6 years of age should be supervised by an adult when applying this product

Keep out of reach of children

If swallowed, get medical help or contact a Poison Control Center right away

Other informatio

- Store between 15-30C (59-86F)
- May discolor certain fabrics or surfaces

Inactive Ingredient

Avocado oil, rosemary oil, glycerin, hydrogen peroxide, purified water USP